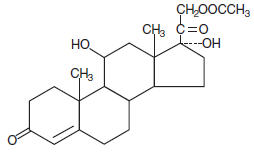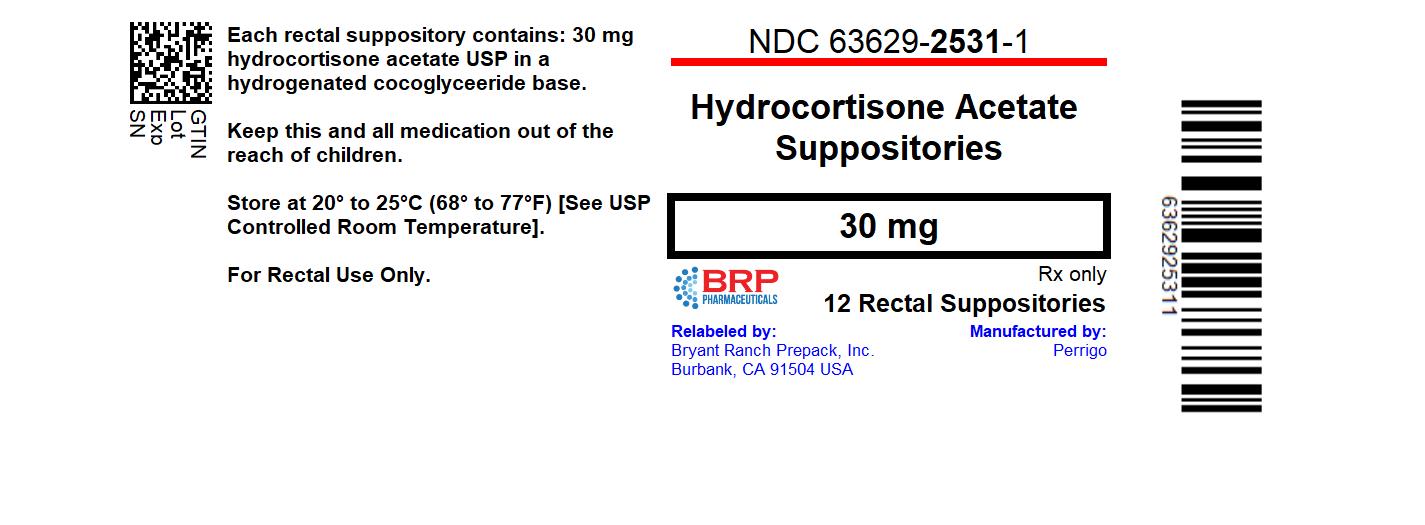 DRUG LABEL: Hydrocortisone Acetate
NDC: 63629-2531 | Form: SUPPOSITORY
Manufacturer: Bryant Ranch Prepack
Category: prescription | Type: HUMAN PRESCRIPTION DRUG LABEL
Date: 20240111

ACTIVE INGREDIENTS: HYDROCORTISONE ACETATE 30 mg/1 1
INACTIVE INGREDIENTS: HYDROGENATED PALM KERNEL OIL

Hydrocortisone Acetate
Suppositories

DESCRIPTION

Each Hydrocortisone Acetate Suppository for rectal administration contains hydrocortisone acetate in a hydrogenated cocoglyceride base.

Hydrocortisone acetate is a corticosteroid. The molecular weight of hydrocortisone acetate is 404.50. Chemically, hydrocortisone acetate is pregn-4-ene-3, 20 dione, 21- (acetyloxy)-11, 17-dihydroxy-, (11β)- with an empirical formula of C23H32O6the following structural formula:

CLINICAL PHARMACOLOGY

In normal subjects, about 26 percent of hydrocortisone acetate is absorbed when the hydrocortisone acetate suppository is applied to the rectum. Absorption of hydrocortisone acetate may vary across abraded or inflamed surfaces.

Topical steroids are primarily effective because of their anti-inflammatory, antipruritic and vasoconstrictive action.

INDICATIONS AND USAGE

Hydrocortisone Acetate Suppositories are indicated for use in inflamed hemorrhoids, post irradiation (factitial) proctitis, as an adjunct in the treatment of chronic ulcerative colitis, cryptitis, other inflammatory conditions of the anorectum, and pruritus ani.

CONTRAINDICATIONS

Hydrocortisone Acetate Suppositories are contraindicated in those patients with a history of hypersensitivity to any of the components.

PRECAUTIONS

Do not use unless adequate proctologic examination is made.

If irritation develops, the product should be discontinued and appropriate therapy instituted.

In the presence of an infection, the use of an appropriate antifungal or antibacterial agent should be instituted. If a favorable response does not occur promptly, the corticosteroid should be discontinued until the infection has been adequately controlled.

Carcinogenesis

No long-term studies in animals have been performed to evaluate the carcinogenic potential of corticosteroid suppositories.

PREGNANCY CATEGORY C

In laboratory animals, topical steroids have been associated with an increase in the incidence of fetal abnormalities when gestating females have been exposed to rather low dosage levels. There are no adequate and well-controlled studies in pregnant women.

Hydrocortisone acetate suppositories should only be used during pregnancy if the potential benefit justifies the risk to the fetus. Drugs of this class should not be used extensively on pregnant patients, in large amounts, or for prolonged periods of time.

It is not known whether this drug is excreted in human milk. Because many drugs are excreted in human milk and because of the potential for serious adverse reactions in nursing infants from hydrocortisone acetate suppositories, a decision should be made whether to discontinue nursing or to discontinue the drug, taking into account the importance of the drug to the mother.

ADVERSE REACTIONS

The following local adverse reactions have been reported with corticosteroid suppositories: burning, itching, irritation, dryness, folliculitis, hypopigmentation, allergic contact dermatitis, and secondary infection.

To report SUSPECTED ADVERSE REACTIONS, contact Perrigo at 1-866-634-9120 or FDA at 1-800-FDA-1088 or www.fda.gov/medwatch.

Drug abuse and dependence have not been reported in patients treated with Hydrocortisone Acetate Suppositories.

OVERDOSAGE

If signs and symptoms of systemic overdosage occur, discontinue use.

DOSAGE AND ADMINISTRATION

Usual dosage: One suppository in the rectum twice daily morning and night for two weeks, in nonspecific proctitis. In more severe cases, one suppository three times daily; or two suppositories twice daily. In factitial proctitis, recommended therapy is six to eight weeks or less, according to the response of the individual case.

HOW SUPPLIED

Hydrocortisone Acetate Suppositories are easy to open, color coded and available in cartons of 12.

30 mg NDC 63629-2531-1

Store at 20° to 25°C (68° to 77°F) [see USP Controlled Room Temperature]. Protect from freezing.

Repackaged/Relabeled by:
Bryant Ranch Prepack, Inc.
Burbank, CA 91504

Rx Only

Manufactured By
Perrigo®
Minneapolis, MN 55427
2201371 1B400 RC J1 Rev 07-19 B

PACKAGE LABEL

Hydrocortisone Acetate 30 mg Suppos #12